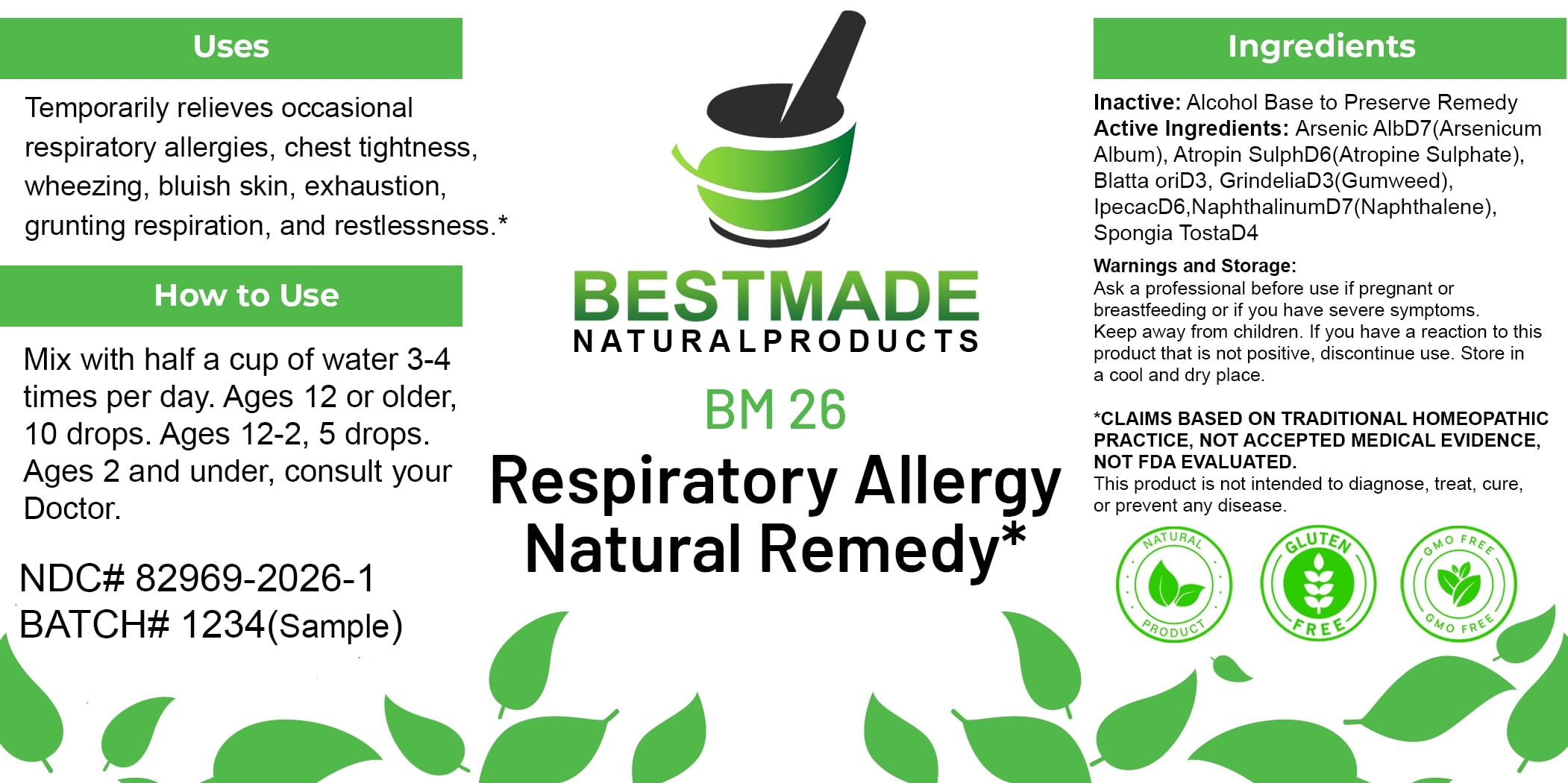 DRUG LABEL: Bestmade Natural Products BM26
NDC: 82969-2026 | Form: LIQUID
Manufacturer: Bestmade Natural Products
Category: homeopathic | Type: HUMAN OTC DRUG LABEL
Date: 20250123

ACTIVE INGREDIENTS: SPONGIA OFFICINALIS SKELETON, ROASTED 30 [hp_C]/30 [hp_C]; NAPHTHALENE 30 [hp_C]/30 [hp_C]; GRINDELIA HIRSUTULA FLOWERING TOP 30 [hp_C]/30 [hp_C]; ARSENIC TRIOXIDE 30 [hp_C]/30 [hp_C]; ATROPINE SULFATE 30 [hp_C]/30 [hp_C]; BLATTA ORIENTALIS 30 [hp_C]/30 [hp_C]; IPECAC 30 [hp_C]/30 [hp_C]
INACTIVE INGREDIENTS: ALCOHOL 30 [hp_C]/30 [hp_C]

BM26

DOSAGE AND ADMINISTRATION

How to Use

Mix with half a cup of water 3-4 times per day. Ages 12 or older, 10 drops. Ages 12-2, 5 drops. Ages 2 and under, consult your Doctor.

INACTIVE INGREDIENT

Ingredients

Inactive: Alcohol Base to Preserve Remedy

Uses

Temporarily relieves occasional respiratory allergies, chest tightness, wheezing, bluish skin, exhaustion, grunting respiration, and restlessness.*

*CLAIMS BASED ON TRADITIONAL HOMEOPATHIC PRACTICE, NOT ACCEPTED MEDICAL EVIDENCE, NOT FDA EVALUATED.

This product is not intended to diagnose, treat, cure, or prevent any disease.

Active Ingredients:

Arsenic AlbD7(Arsenicum Album), Atropin SulphD6(Atropine Sulphate), Blatta oriD3, GrindeliaD3(Gumweed), IpecacD6, NaphthalinumD7(Naphthalene), Spongia TostaD4

Uses

Temporarily relieves occasional respiratory allergies, chest tightness, wheezing, bluish skin, exhaustion, grunting respiration, and restlessness.*

*CLAIMS BASED ON TRADITIONAL HOMEOPATHIC PRACTICE, NOT ACCEPTED MEDICAL EVIDENCE, NOT FDA EVALUATED.

This product is not intended to diagnose, treat, cure, or prevent any disease.

KEEP OUT OF REACH OF CHILDREN

Warnings and Storage:

Ask a professional before use if pregnant or breastfeeding or if you have severe symptoms. Keep away from children. If you have a reaction to this product that is not positive, discontinue use. Store in a cool and dry place.

Warnings and Storage:

Ask a professional before use if pregnant or breastfeeding or if you have severe symptoms. Keep away from children. If you have a reaction to this product that is not positive, discontinue use. Store in a cool and dry place.

*CLAIMS BASED ON TRADITIONAL HOMEOPATHIC PRACTICE, NOT ACCEPTED MEDICAL EVIDENCE, NOT FDA EVALUATED.

This product is not intended to diagnose, treat, cure, or prevent any disease.

Entire package label